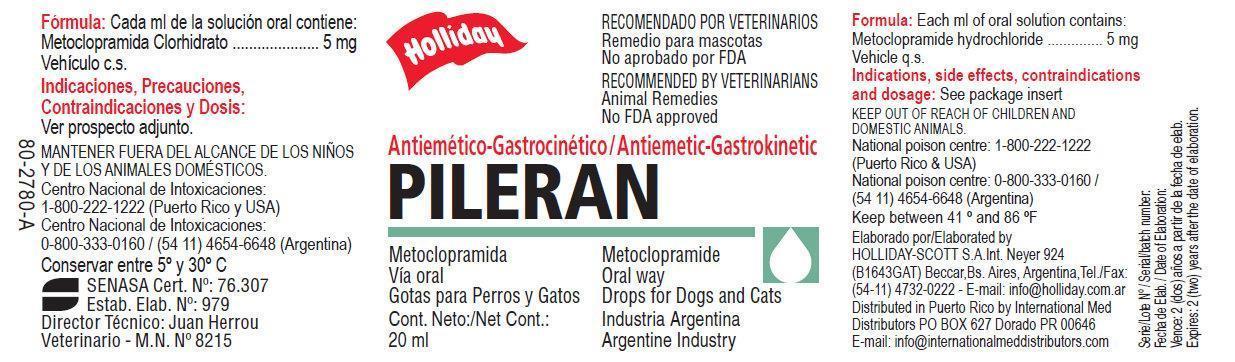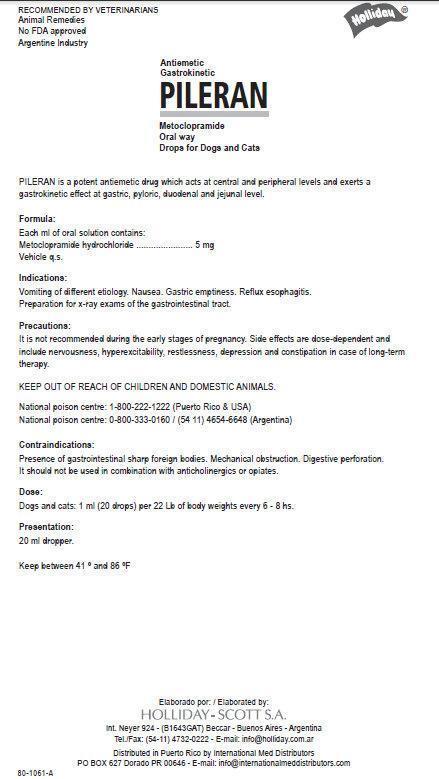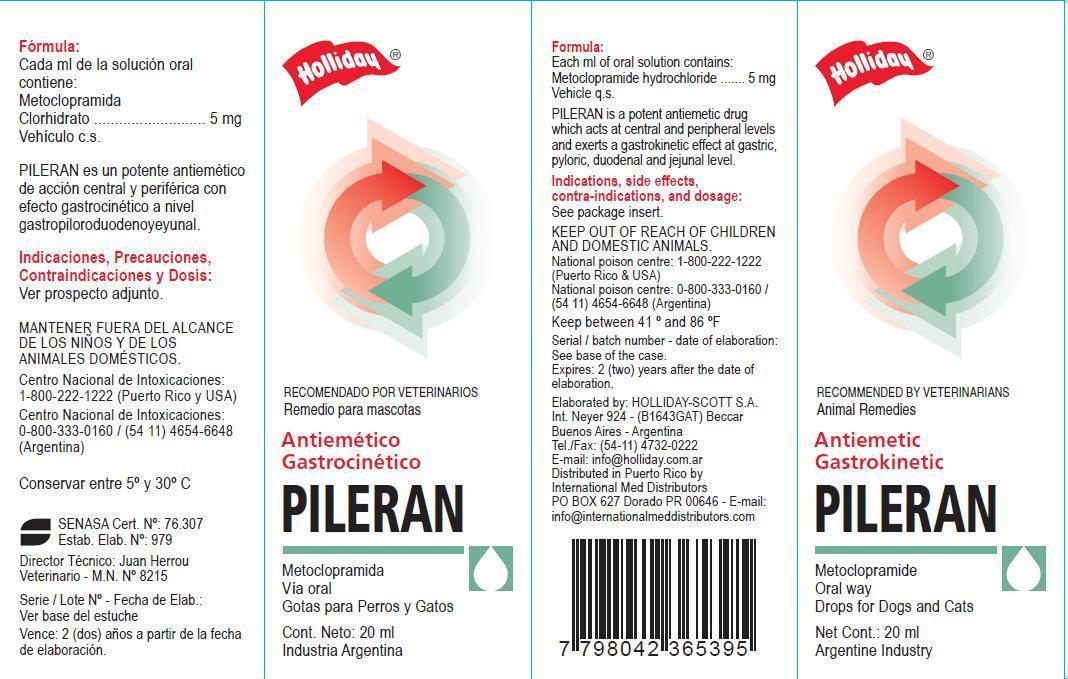 DRUG LABEL: Antiemetic Gastrokinetic PILERAN
                
NDC: 58670-001 | Form: SOLUTION
Manufacturer: Holliday-Scott S.A.
Category: animal | Type: OTC ANIMAL DRUG LABEL
Date: 20130718

ACTIVE INGREDIENTS: METOCLOPRAMIDE HYDROCHLORIDE 5 mg/1 mL

Antiemetic Gastrokinetic PILERAN

Antiemetic Gastrokinetic PILERAN

Metoclopramide Oral way Drops for dogs and Cats. PILERAN is a potent antiemetic drug which acts at central and peripheral levels and exerts a gastrokinetic effect at gastric, pyloric, duodenal and jejunal level.

Formula:

Each ml of oral solution contains:
Metoclopramide hydrochloride...........5 mg Vehicle q.s.

Indications:

Vomiting of different etiology. Nausea. Gastric emptiness. Reflux espphagitis Preparation for x-ray exams of the gastrointestinal tract.

Precautions:

It is not recommended during the early stages of pregnancy. Side effects are dose-dependent and include nervousness, hyperexcitability, restlessness, depression and constipation in case of long-term therapy.

KEEP OUT OF REACH OF CHILDREN.

National poison centre: 1-800-222-1222 (Puerto Rico and USA)
National poison centre: 0-800-333-0160 / (54 11) 4654-6648 (Argentina)

Contraindications:

Presence of gastrointestinal sharp foreign bodies. Mechanical obstruction. Digestive perforation. It should not be used in combination with anticholinergics or opiates.

Dose:

Dogs and cats: 1 ml (20 drops) per 22 Lb of body weight every 6 - 8 hs.

Presentation:

20 ml dropper

Keep between 41 degree and 86 degree F

Elaborated by:

HOLLIDAY-SCOTT S.A.
Int. Neyer 924 - (B1643GAT) Beccar
Buenos Aires - Argentina

Tel./Fax: (54-11) 4732-0222
E-mail: info@holliday.com.ar
Distributed in Puerto Rico by
International Med Distributors
PO BOX 627 Dorado PR 00646 - E-mail:
info@internationalmeddistributors.com

7 798042 365395